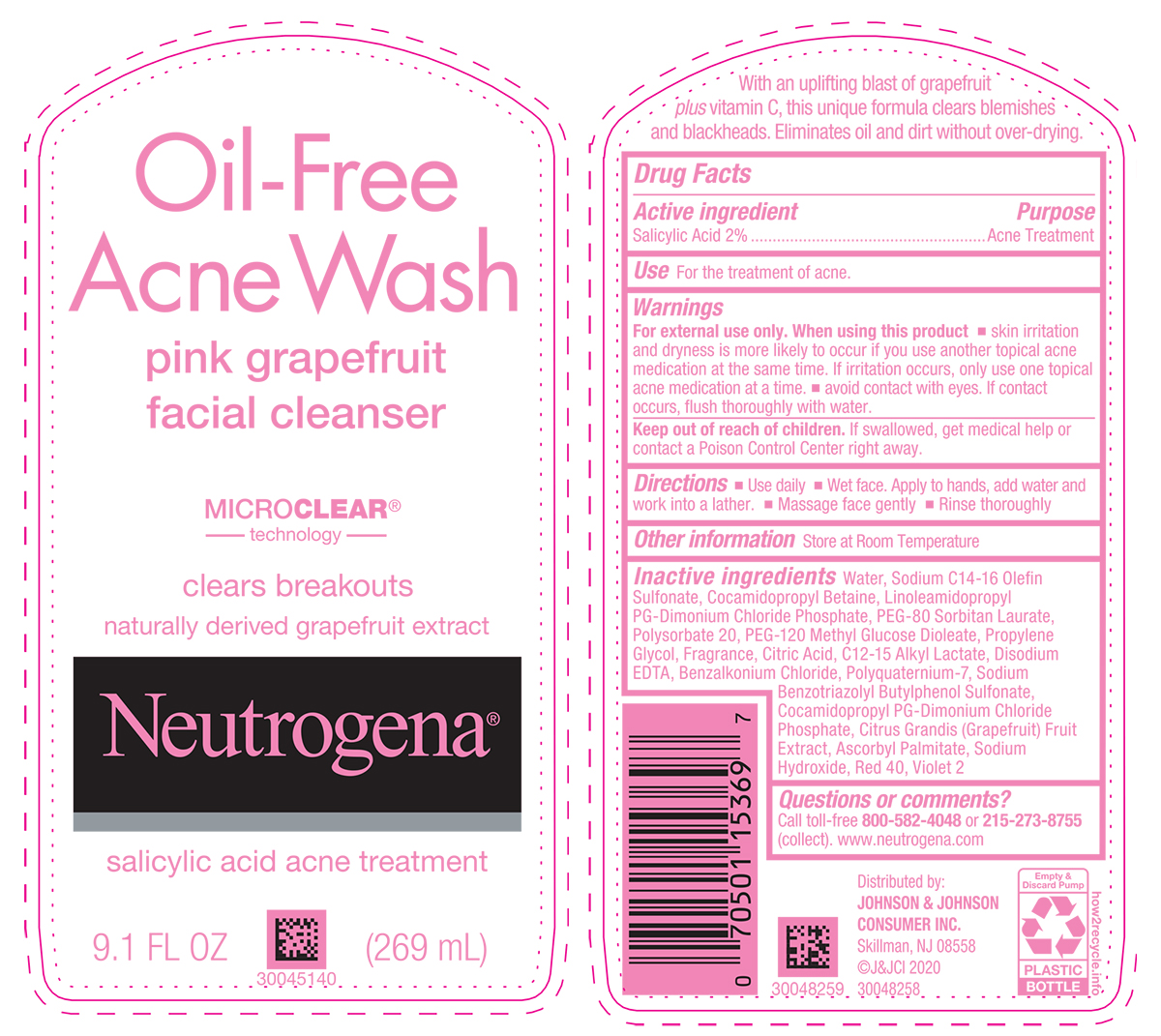 DRUG LABEL: Neutrogena Oil Free Acne Wash Pink Grapefruit Facial Cleanser
NDC: 69968-0686 | Form: LIQUID
Manufacturer: Kenvue Brands LLC
Category: otc | Type: HUMAN OTC DRUG LABEL
Date: 20241112

ACTIVE INGREDIENTS: SALICYLIC ACID 20 mg/1 mL
INACTIVE INGREDIENTS: WATER; SODIUM C14-16 OLEFIN SULFONATE; COCAMIDOPROPYL BETAINE; LINOLEAMIDOPROPYL PROPYLENE GLYCOL-DIMONIUM CHLORIDE PHOSPHATE; PEG-80 SORBITAN LAURATE; POLYSORBATE 20; PEG-120 METHYL GLUCOSE DIOLEATE; PROPYLENE GLYCOL; CITRIC ACID MONOHYDRATE; C12-15 ALKYL LACTATE; EDETATE DISODIUM; BENZALKONIUM CHLORIDE; POLYQUATERNIUM-7 (70/30 ACRYLAMIDE/DADMAC; 1600000 MW); SODIUM BENZOTRIAZOLYL BUTYLPHENOL SULFONATE; COCAMIDOPROPYL PROPYLENE GLYCOL-DIMONIUM CHLORIDE PHOSPHATE; PUMMELO; ASCORBYL PALMITATE; SODIUM HYDROXIDE; FD&C RED NO. 40; D&C VIOLET NO. 2

Neutrogena® Oil-Free Acne Wash pink grapefruit facial cleanser

Drug Facts

Active ingredient

Salicylic Acid 2%

Purpose

Acne Treatment

Use

For the treatment of acne.

Warnings

For external use only.

When using this product

- skin irritation and dryness is more likely to occur if you use another topical acne medication at the same time. If irritation occurs, only use one topical acne medication at a time.
- avoid contact with eyes. If contact occurs, flush thoroughly with water.

Keep out of reach of children. If swallowed, get medical help or contact a Poison Control Center right away.

Directions

- Use daily
- Wet face. Apply to hands, add water and work into a lather.
- Massage face gently
- Rinse thoroughly.

Other information

Store at Room Temperature

Inactive ingredients

Water, Sodium C14-16 Olefin Sulfonate, Cocamidopropyl Betaine, Linoleamidopropyl PG-Dimonium Chloride Phosphate, PEG-80 Sorbitan Laurate, Polysorbate 20, PEG-120 Methyl Glucose Dioleate, Propylene Glycol, Fragrance, Citric Acid, C12-15 Alkyl Lactate, Disodium EDTA, Benzalkonium Chloride, Polyquaternium-7, Sodium Benzotriazolyl Butylphenol Sulfonate, Cocamidopropyl PGDimonium Chloride Phosphate, Citrus Grandis (Grapefruit) Fruit Extract, Ascorbyl Palmitate, Sodium Hydroxide, Red 40, Violet 2

Questions or comments?

Call toll-free 800-582-4048 or 215-273-8755 (collect). www.neutrogena.com

Distributed by: JOHNSON & JOHNSON
CONSUMER INC. Skillman, NJ 08558

PRINCIPAL DISPLAY PANEL - 177 mL Bottle Label

Oil-Free
Acne Wash
pink grapefruit
facial cleanser
MICRO CLEAR®
technology
clear breakouts
naturally derived grapefruit extract
Neutrogena®
salicylic acid acne treatment
9.1 FL OZ (269 mL)